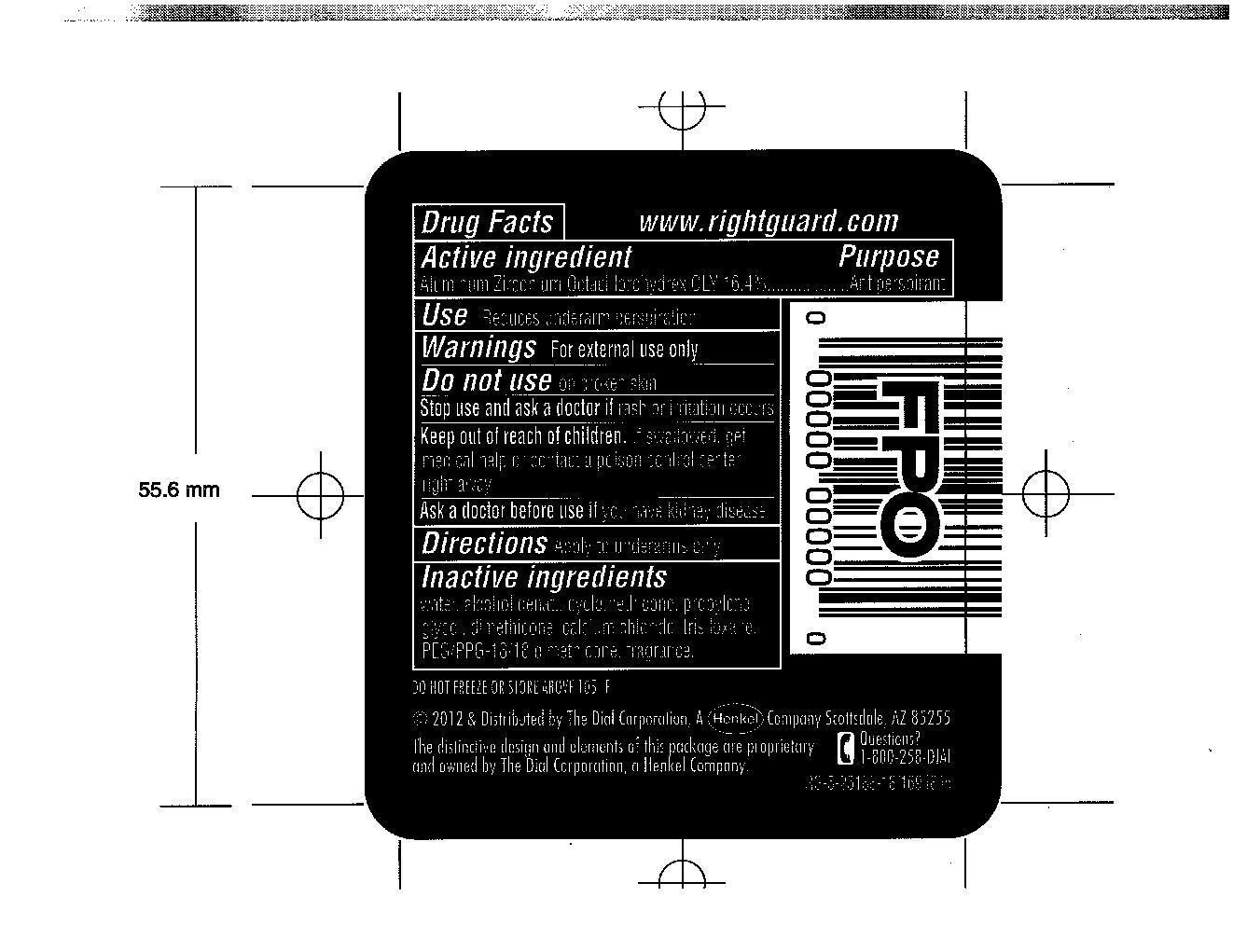 DRUG LABEL: Right Guard Sport
NDC: 51815-209 | Form: GEL
Manufacturer: VVF Illinois Services
Category: otc | Type: HUMAN OTC DRUG LABEL
Date: 20140320

ACTIVE INGREDIENTS: ALUMINUM ZIRCONIUM OCTACHLOROHYDREX GLY 13.94 1/85 g
INACTIVE INGREDIENTS: Water; ALCOHOL; CYCLOMETHICONE; PROPYLENE GLYCOL; DIMETHICONE; CALCIUM CHLORIDE; TRISILOXANE; PEG/PPG-18/18 DIMETHICONE

Right Guard Sport Fresh

Active Ingredient

Aluminum Zirconium Octachlorohydrex GLY 16.4%

Purpose

Antiperspirant

Warnings

For external use only

Stop use and ask a doctor if rash or irritation occurs

Keep out of reach of children

If swallowed, get medical help or contact a poison control center right away.

Use

Reduces underarm perspiration

Ask a doctor before use if you have kidney disease

Inactive ingredients

Water, alcohol denat, cyclomethicone, propylene glycol, dimethicone, calcium chloride, trisiloxane, PEG/PPG-18/18 Dimethicone, Fragrance.

QUESTIONS

Call 1-800-258-DIAL

Directions

Apply to underarms only.